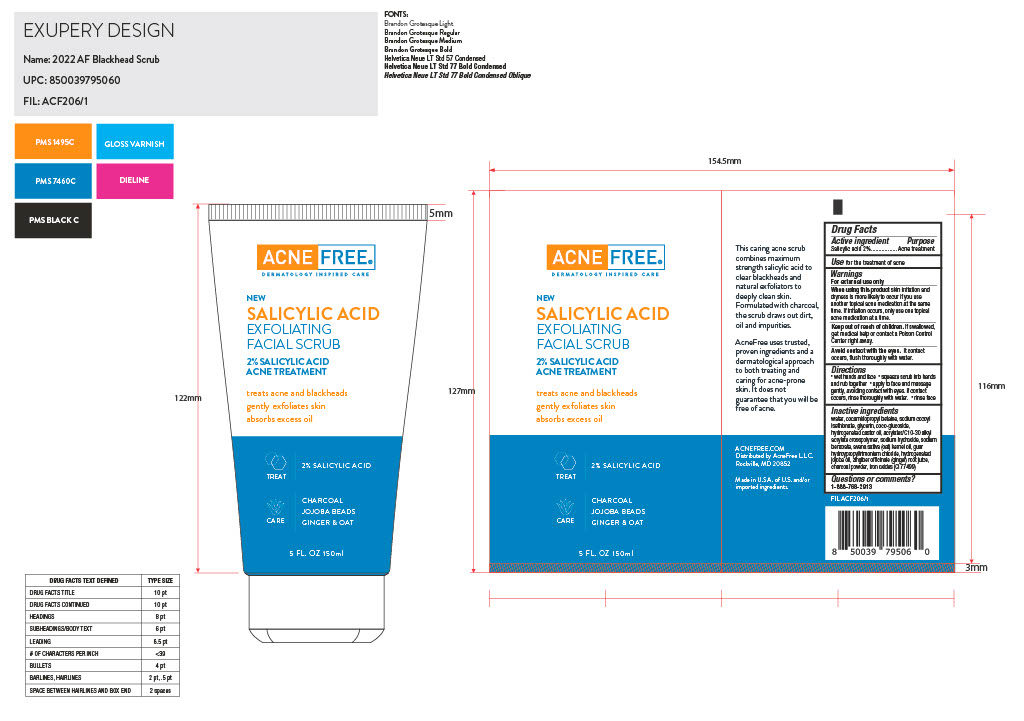 DRUG LABEL: Salicylic Acid
NDC: 80861-117 | Form: CREAM
Manufacturer: Acne Free, LLC
Category: otc | Type: HUMAN OTC DRUG LABEL
Date: 20250724

ACTIVE INGREDIENTS: SALICYLIC ACID 0.02 g/1 g
INACTIVE INGREDIENTS: COCAMIDOPROPYL BETAINE

Acne Free Salicylic Acid Exfoliating Scrub

Active Ingredient

Salicylic Acid 2%

Purpose

Acne treatment

Use

Use for the treatment of acne

Warnings

For external use only

When using this product skin irritation and dryness is more likely to occur if you use another topical acne medication at the same time. If irritation occurs, only use one topical acne medication at a time.

Keep out of reach of children. If swallowed, get medical help or contact a Poison Control Center right away.

Avoid contact with eyes

Avoid contact with the eyes. It contact occurs, ush thoroughly with water.

Directions

wet hands and face • squeeze scrub into hands and rub together • apply to face and massage gently, avoiding contact with eyes. If contact occurs, rinse thoroughly with water. • rinse face

Inactive Ingredients

water, cocamidopropyl betaine, sodium cocoyl isethionate, glycerin, coco-glucoside, hydrogenated castor oil, acrylates/C10-30 alkyl acrylate crosspolymer, sodium hydroxide, sodium benzoate, avena sativa (oat) kernel oil, guar hydroypropyltrimonium chloride, hydrogenated jojoba oil, zingiber of cinale (ginger) root juice, charcoal powder, iron oxides (CI 77499)

Questions or comments?

1-888-768-2913